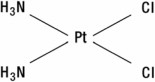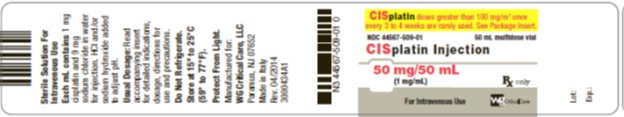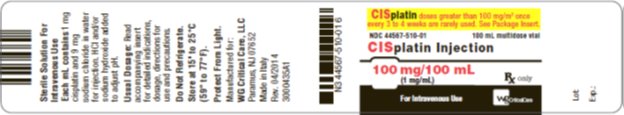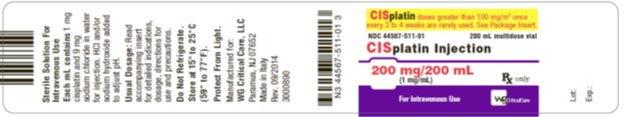 DRUG LABEL: CISplatin
NDC: 44567-509 | Form: INJECTION, SOLUTION
Manufacturer: WG Critical Care, LLC
Category: prescription | Type: HUMAN PRESCRIPTION DRUG LABEL
Date: 20210916

ACTIVE INGREDIENTS: cisplatin 1 mg/1 mL
INACTIVE INGREDIENTS: Sodium Chloride; Hydrochloric Acid; Sodium Hydroxide; Water

CISplatin Injection

Rx only

WARNING

Cisplatin Injection should be administered under the supervision of a qualified physician experienced in the use of cancer chemotherapeutic agents. Appropriate management of therapy and complications is possible only when adequate diagnostic and treatment facilities are readily available.

Cumulative renal toxicity associated with cisplatin is severe. Other major dose-related toxicities are myelosuppression, nausea, and vomiting.

Ototoxicity, which may be more pronounced in children, and is manifested by tinnitus, and/or loss of high frequency hearing and occasionally deafness, is significant.

Anaphylactic-like reactions to cisplatin have been reported. Facial edema, bronchoconstriction, tachycardia, and hypotension may occur within minutes of cisplatin administration. Epinephrine, corticosteroids, and antihistamines have been effectively employed to alleviate symptoms (see WARNINGS and ADVERSE REACTIONS sections).

Exercise caution to prevent inadvertent cisplatin overdose. Doses greater than 100 mg/m^2/cycle once every 3 to 4 weeks are rarely used. Care must be taken to avoid inadvertent cisplatin overdose due to confusion with carboplatin or prescribing practices that fail to differentiate daily doses from total dose per cycle.

DESCRIPTION

Cisplatin Injection infusion concentrate is a clear, colorless, sterile aqueous solution available in amber vials. Each 50 mL, 100 mL or 200 mL amber vial of infusion concentrate contains: 1 mg/mL cisplatin, 9 mg/mL sodium chloride, hydrochloric acid and sodium hydroxide to approximate pH of 4.0, and water for injection to a final volume of 50 mL, 100 mL or 200 mL respectively.

Cisplatin Injection infusion concentrate must be further diluted prior to administration (see DOSAGE AND ADMINISTRATION, All Patients).

The active ingredient, cisplatin, is a yellow to orange crystalline powder with the molecular formula PtCl2H6N2, and a molecular weight of 300.1. Cisplatin is a heavy metal complex containing a central atom of platinum surrounded by two chloride atoms and two ammonia molecules in the cis position. It is soluble in water or saline at 1 mg/mL and in dimethylformamide at 24 mg/mL. It has a melting point of 207° C.

CLINICAL PHARMACOLOGY

Plasma concentrations of the parent compound, cisplatin, decay monoexponentially with a half-life of about 20 to 30 minutes following bolus administrations of 50 or 100 mg/m^2 doses. Monoexponential decay and plasma half-lives of about 0.5 hour are also seen following 2-hour or 7-hour infusions of 100 mg/m^2. After the latter, the total-body clearances and volumes of distribution at steady-state for cisplatin are about 15 to 16 L/h/m^2 and 11 to 12 L/m^2.

Due to its unique chemical structure, the chlorine atoms of cisplatin are more subject to chemical displacement reactions by nucleophiles, such as water or sulfhydryl groups, than to enzyme-catalyzed metabolism. At physiological pH in the presence of 0.1M NaCl, the predominant molecular species are cisplatin and monohydroxymonochloro cis-diammine platinum (II) in nearly equal concentrations. The latter, combined with the possible direct displacement of the chlorine atoms by sulfhydryl groups of amino acids or proteins, accounts for the instability of cisplatin in biological matrices. The ratios of cisplatin to total free (ultrafilterable) platinum in the plasma vary considerably between patients and range from 0.5 to 1.1 after a dose of 100 mg/m^2.

Cisplatin does not undergo the instantaneous and reversible binding to plasma proteins that is characteristic of normal drug-protein binding. However, the platinum from cisplatin, but not cisplatin itself, becomes bound to several plasma proteins, including albumin, transferrin, and gamma globulin. Three hours after a bolus injection and two hours after the end of a three-hour infusion, 90% of the plasma platinum is protein bound. The complexes between albumin and the platinum from cisplatin do not dissociate to a significant extent and are slowly eliminated with a minimum half-life of five days or more.

Following cisplatin doses of 20 to 120 mg/m^2, the concentrations of platinum are highest in liver, prostate, and kidney; somewhat lower in bladder, muscle, testicle, pancreas, and spleen; and lowest in bowel, adrenal, heart, lung, cerebrum, and cerebellum. Platinum is present in tissues for as long as 180 days after the last administration. With the exception of intracerebral tumors, platinum concentrations in tumors are generally somewhat lower than the concentrations in the organ where the tumor is located. Different metastatic sites in the same patient may have different platinum concentrations. Hepatic metastases have the highest platinum concentrations, but these are similar to the platinum concentrations in normal liver. Maximum red blood cell concentrations of platinum are reached within 90 to 150 minutes after a 100 mg/m^2 dose of cisplatin and decline in a biphasic manner with a terminal half-life of 36 to 47 days.

Over a dose range of 40 to 140 mg cisplatin/m^2 given as a bolus injection or as infusions varying in length from 1 hour to 24 hours, from 10% to about 40% of the administered platinum is excreted in the urine in 24 hours. Over five days following administration of 40 to 100 mg/m^2 doses given as rapid, 2- to 3-hour, or 6- to 8-hour infusions, a mean of 35% to 51% of the dosed platinum is excreted in the urine. Similar mean urinary recoveries of platinum of about 14% to 30% of the dose are found following five daily administrations of 20, 30, or 40 mg/m^2/day. Only a small percentage of the administered platinum is excreted beyond 24 hours post-infusion and most of the platinum excreted in the urine in 24 hours is excreted within the first few hours. Platinum-containing species excreted in the urine are the same as those found following the incubation of cisplatin with urine from healthy subjects, except that the proportions are different.

The parent compound, cisplatin, is excreted in the urine and accounts for 13% to 17% of the dose excreted within one hour after administration of 50 mg/m^2. The mean renal clearance of cisplatin exceeds creatinine clearance and is 62 and 50 mL/min/m^2 following administration of 100 mg/m^2 as 2-hour or 6- to 7-hour infusions, respectively.

The renal clearance of free (ultrafilterable) platinum also exceeds the glomerular filtration rate indicating that cisplatin or other platinum-containing molecules are actively secreted by the kidneys. The renal clearance of free platinum is nonlinear and variable and is dependent on dose, urine flow rate, and individual variability in the extent of active secretion and possible tubular reabsorption.

There is a potential for accumulation of ultrafilterable platinum plasma concentrations whenever cisplatin is administered on a daily basis but not when dosed on an intermittent basis.

No significant relationships exist between the renal clearance of either free platinum or cisplatin and creatinine clearance.

Although small amounts of platinum are present in the bile and large intestine after administration of cisplatin, the fecal excretion of platinum appears to be insignificant.

INDICATIONS

Cisplatin Injection is indicated as therapy to be employed as follows:

Metastatic Testicular Tumors

In established combination therapy with other approved chemotherapeutic agents in patients with metastatic testicular tumors who have already received appropriate surgical and/or radiotherapeutic procedures.

Metastatic Ovarian Tumors

In established combination therapy with other approved chemotherapeutic agents in patients with metastatic ovarian tumors who have already received appropriate surgical and/or radiotherapeutic procedures. An established combination consists of Cisplatin Injection and cyclophosphamide. Cisplatin Injection, as a single agent, is indicated as secondary therapy in patients with metastatic ovarian tumors refractory to standard chemotherapy who have not previously received Cisplatin Injection therapy.

Advanced Bladder Cancer

Cisplatin Injection is indicated as a single agent for patients with transitional cell bladder cancer which is no longer amenable to local treatments, such as surgery and/or radiotherapy.

CONTRAINDICATIONS

Cisplatin is contraindicated in patients with preexisting renal impairment. Cisplatin should not be employed in myelosuppressed patients, or in patients with hearing impairment.

Cisplatin is contraindicated in patients with a history of allergic reactions to cisplatin or other platinum-containing compounds.

WARNINGS

Cisplatin produces cumulative nephrotoxicity which is potentiated by aminoglycoside antibiotics. The serum creatinine, blood urea nitrogen (BUN), creatinine clearance, and magnesium, sodium, potassium, and calcium levels should be measured prior to initiating therapy, and prior to each subsequent course. At the recommended dosage, cisplatin should not be given more frequently than once every 3 to 4 weeks (see ADVERSE REACTIONS). Elderly patients may be more susceptible to nephrotoxicity (see PRECAUTIONS, Geriatric Use).

There are reports of severe neuropathies in patients in whom regimens are employed using higher doses of cisplatin or greater dose frequencies than those recommended. These neuropathies may be irreversible and are seen as paresthesias in a stocking-glove distribution, areflexia, and loss of proprioception and vibratory sensation. Elderly patients may be more susceptible to peripheral neuropathy (see PRECAUTIONS, Geriatric Use).

Loss of motor function has also been reported.

Anaphylactic-like reactions to cisplatin have been reported. These reactions have occurred within minutes of administration to patients with prior exposure to cisplatin, and have been alleviated by administration of epinephrine, corticosteroids, and antihistamines.

Cisplatin can commonly cause ototoxicity which is cumulative and may be severe. Audiometric testing should be performed prior to initiating therapy and prior to each subsequent dose of drug (see ADVERSE REACTIONS).

All pediatric patients receiving cisplatin should have audiometric testing at baseline, prior to each subsequent dose, of drug and for several years post therapy.

Cisplatin can cause fetal harm when administered to a pregnant woman. Cisplatin is mutagenic in bacteria and produces chromosome aberrations in animal cells in tissue culture. In mice cisplatin is teratogenic and embryotoxic. If this drug is used during pregnancy or if the patient becomes pregnant while taking this drug, the patient should be apprised of the potential hazard to the fetus. Patients should be advised to avoid becoming pregnant.

The carcinogenic effect of cisplatin was studied in BD IX rats. Cisplatin was administered intraperitoneally (i.p.) to 50 BD IX rats for 3 weeks, 3 X 1 mg/kg body weight per week. Four hundred and fifty-five days after the first application, 33 animals died, 13 of them related to malignancies: 12 leukemias and 1 renal fibrosarcoma.

The development of acute leukemia coincident with the use of cisplatin has been reported. In these reports, cisplatin was generally given in combination with other leukemogenic agents.

Injection site reactions may occur during the administration of cisplatin (see ADVERSE REACTIONS). Given the possibility of extravasation, it is recommended to closely monitor the infusion site for possible infiltration during drug administration. A specific treatment for extravasation reactions is unknown at this time.

PRECAUTIONS

Peripheral blood counts should be monitored weekly. Liver function should be monitored periodically. Neurologic examination should also be performed regularly (see ADVERSE REACTIONS).

Drug Interactions

Plasma levels of anticonvulsant agents may become subtherapeutic during cisplatin therapy.

In a randomized trial in advanced ovarian cancer, response duration was adversely affected when pyridoxine was used in combination with altretamine (hexamethylmelamine) and cisplatin.

Carcinogenesis, Mutagenesis, Impairment of Fertility

See WARNINGS.

Pregnancy Category D

See WARNINGS.

Nursing Mothers

Cisplatin has been reported to be found in human milk; patients receiving cisplatin should not breast-feed.

Pediatric Use

Safety and effectiveness in pediatric patients have not been established.

All children should have audiometric monitoring performed prior to initiation of therapy prior to each subsequent dose, and for several years post therapy. Advanced testing methods may allow for earlier detection of hearing loss in an attempt to facilitate the rapid initiation of interventions that can limit the potential adverse impact of hearing impairment on a child's cognitive and social development.

Geriatric Use

Insufficient data are available from clinical trials of cisplatin in the treatment of metastatic testicular tumors or advanced bladder cancer to determine whether elderly patients respond differently than younger patients. In four clinical trials of combination chemotherapy for advanced ovarian carcinoma, 1484 patients received cisplatin either in combination with cyclophosphamide or paclitaxel. Of these, 426 (29%) were older than 65 years. In these trials, age was not found to be a prognostic factor for survival. However, in a later secondary analysis for one of these trials, elderly patients were found to have shorter survival compared with younger patients. In all four trials, elderly patients experienced more severe neutropenia than younger patients. Higher incidences of severe thrombocytopenia and leukopenia were also seen in elderly compared with younger patients, although not in all cisplatin-containing treatment arms. In the two trials where nonhematologic toxicity was evaluated according to age, elderly patients had a numerically higher incidence of peripheral neuropathy than younger patients. Other reported clinical experience suggests that elderly patients may be more susceptible to myelosuppression, infectious complications, and nephrotoxicity than younger patients.

Cisplatin is known to be substantially excreted by the kidney and is contraindicated in patients with preexisting renal impairment. Because elderly patients are more likely to have decreased renal function, care should be taken in dose selection, and renal function should be monitored.

ADVERSE REACTIONS

Nephrotoxicity

Dose-related and cumulative renal insufficiency, including acute renal failure, is the major dose-limiting toxicity of cisplatin. Renal toxicity has been noted in 28% to 36% of patients treated with a single dose of 50 mg/m^2. It is first noted during the second week after a dose and is manifested by elevations in BUN and creatinine, serum uric acid and/or a decrease in creatinine clearance. Renal toxicity becomes more prolonged and severe with repeated courses of the drug. Renal function must return to normal before another dose of cisplatin can be given. Elderly patients may be more susceptible to nephrotoxicity (see PRECAUTIONS, Geriatric Use).

Impairment of renal function has been associated with renal tubular damage. The administration of cisplatin using a 6- to 8-hour infusion with intravenous hydration, and mannitol has been used to reduce nephrotoxicity. However, renal toxicity still can occur after utilization of these procedures.

Ototoxicity

Ototoxicity has been observed in up to 31% of patients treated with a single dose of cisplatin 50 mg/m^2, and is manifested by tinnitus and/or hearing loss in the high frequency range (4000 to 8000 Hz). The prevelance of hearing loss in children is particularly high and is estimated to be 40-60%. Decreased ability to hear normal conversational tones may occur. Deafness after the initial dose of cisplatin has been reported. Ototoxic effects may be more severe in children receiving cisplatin.

Hearing loss can be unilateral or bilateral and tends to become more frequent and severe with repeated cisplatin doses. It is unclear whether cisplatin-induced ototoxicity is reversible. Vestibular toxicity has also been reported. Ototoxic effects may be related to the peak plasma concentration of cisplatin. Ototoxicity can occur during treatment or be delayed. Audiometric monitoring should be performed prior to initiation of therapy, prior to each subsequent dose, and for several years post therapy.

The risk of ototoxicity may be increased by prior or simultaneous cranial irradiation, and may be more severe in patients less than 5 years of age, patients being treated with other ototoxic drugs (e.g. aminoglycosides and vancomycin), and in patients with renal impairment.

Genetic factors (e.g. variants in the thiopurine S-methyltransferase [TPMT] gene) may contribute to cisplatin-induced ototoxicity; although this association has not been consistent across populations and study designs.

Hematologic

Myelosuppression occurs in 25% to 30% of patients treated with cisplatin. The nadirs in circulating platelets and leukocytes occur between days 18 to 23 (range 7.5 to 45) with most patients recovering by day 39 (range 13 to 62). Leukopenia and thrombocytopenia are more pronounced at higher doses (>50 mg/m^2). Anemia (decrease of 2 g hemoglobin/100 mL) occurs at approximately the same frequency and with the same timing as leukopenia and thrombocytopenia. Fever and infection have also been reported in patients with neutropenia. Potential fatalities due to infection (secondary to myelosuppression) have been reported. Elderly patients may be more susceptible to myelosuppression (see PRECAUTIONS, Geriatric Use).

In addition to anemia secondary to myelosuppression, a Coombs' positive hemolytic anemia has been reported. In the presence of cisplatin hemolytic anemia, a further course of treatment may be accompanied by increased hemolysis and this risk should be weighed by the treating physician.

The development of acute leukemia coincident with the use of cisplatin has been reported. In these reports, cisplatin was generally given in combination with other leukemogenic agents.

Gastrointestinal

Marked nausea and vomiting occur in almost all patients treated with cisplatin, and may be so severe that the drug must be discontinued. Nausea and vomiting may begin within 1 to 4 hours after treatment and last up to 24 hours. Various degrees of vomiting, nausea and/or anorexia may persist for up to 1 week after treatment.

Delayed nausea and vomiting (begins or persists 24 hours or more after chemotherapy) has occurred in patients attaining complete emetic control on the day of cisplatin therapy.

Diarrhea has also been reported.

To report SUSPECTED ADVERSE REACTIONS, contact WG Critical Care, LLC at 1-866-562-4708 or FDA at 1-800-FDA-1088 or www.fda.gov/medwatch.

OTHER TOXICITIES

Vascular toxicities coincident with the use of cisplatin in combination with other antineoplastic agents have been reported. The events are clinically heterogeneous and may include myocardial infarction, cerebrovascular accident, thrombotic microangiopathy (hemolytic-uremic syndrome [HUS]), or cerebral arteritis. Various mechanisms have been proposed for these vascular complications. There are also reports of Raynaud's phenomenon occurring in patients treated with the combination of bleomycin, vinblastine with or without cisplatin. It has been suggested that hypomagnesemia developing coincident with the use of cisplatin may be an added, although not essential, factor associated with this event. However, it is currently unknown if the cause of Raynaud's phenomenon in these cases is the disease, underlying vascular compromise, bleomycin, vinblastine, hypomagnesemia, or a combination of any of these factors.

Serum Electrolyte Disturbances

Hypomagnesemia, hypocalcemia, hyponatremia, hypokalemia, and hypophosphatemia have been reported to occur in patients treated with cisplatin and are probably related to renal tubular damage. Tetany has been reported in those patients with hypocalcemia and hypomagnesemia. Generally, normal serum electrolyte levels are restored by administering supplemental electrolytes and discontinuing cisplatin.

Inappropriate antidiuretic hormone syndrome has also been reported.

Hyperuricemia

Hyperuricemia has been reported to occur at approximately the same frequency as the increases in BUN and serum creatinine.

It is more pronounced after doses greater than 50 mg/m^2, and peak levels of uric acid generally occur between 3 to 5 days after the dose. Allopurinol therapy for hyperuricemia effectively reduces uric acid levels.

Neurotoxicity

See WARNINGS.

Neurotoxicity, usually characterized by peripheral neuropathies, has been reported. The neuropathies usually occur after prolonged therapy (4 to 7 months); however, neurologic symptoms have been reported to occur after a single dose. Although symptoms and signs of cisplatin neuropathy usually develop during treatment, symptoms of neuropathy may begin 3 to 8 weeks after the last dose of cisplatin. Cisplatin therapy should be discontinued when the symptoms are first observed. The neuropathy, however, may progress further even after stopping treatment. Preliminary evidence suggests peripheral neuropathy may be irreversible in some patients. Elderly patients may be more susceptible to peripheral neuropathy (see PRECAUTIONS, Geriatric Use).

Lhermitte's sign, dorsal column myelopathy, and autonomic neuropathy have also been reported.

Loss of taste, seizures, leukoencephalopathy, and reversible posterior leukoencephalopathy syndrome (RPLS) have also been reported.

Muscle cramps, defined as localized, painful, involuntary skeletal muscle contractions of sudden onset and short duration, have been reported and were usually associated in patients receiving a relatively high cumulative dose of cisplatin and with a relatively advanced symptomatic stage of peripheral neuropathy.

Ocular Toxicity

Optic neuritis, papilledema, and cerebral blindness have been reported in patients receiving standard recommended doses of cisplatin. Improvement and/or total recovery usually occurs after discontinuing cisplatin. Steroids with or without mannitol have been used; however, efficacy has not been established.

Blurred vision and altered color perception have been reported after the use of regimens with higher doses of cisplatin or greater dose frequencies than recommended in the package insert. The altered color perception manifests as a loss of color discrimination, particularly in the blue-yellow axis. The only finding on funduscopic exam is irregular retinal pigmentation of the macular area.

Anaphylactic-like reactions have been reported in patients previously exposed to cisplatin. The reactions consist of facial edema, wheezing, tachycardia, and hypotension within a few minutes of drug administration. Reactions may be controlled by intravenous epinephrine with corticosteroids and/or antihistamines as indicated. Patients receiving cisplatin should be observed carefully for possible anaphylactic-like reactions and supportive equipment and medication should be available to treat such a complication.

Hepatotoxicity

Transient elevations of liver enzymes, especially SGOT, as well as bilirubin, have been reported to be associated with cisplatin administration at the recommended doses.

Other Events

Cardiac abnormalities, hiccups, elevated serum amylase, rash, alopecia, malaise, asthenia, and dehydration have been reported.

Local soft tissue toxicity has been reported following extravasation of cisplatin. Severity of the local tissue toxicity appears to be related to the concentration of the cisplatin solution. Infusion of solutions with a cisplatin concentration greater than 0.5 mg/mL may result in tissue cellulitis, fibrosis, necrosis, pain, edema, and erythema.

OVERDOSAGE

Caution should be exercised to prevent inadvertent overdosage with cisplatin. Acute overdosage with this drug may result in kidney failure, liver failure, deafness, ocular toxicity (including detachment of the retina), significant myelosuppression, intractable nausea and vomiting and/or neuritis. In addition, death can occur following overdosage.

No proven antidotes have been established for cisplatin overdosage. Hemodialysis, even when initiated four hours after the overdosage, appears to have little effect on removing platinum from the body because of cisplatin's rapid and high degree of protein binding. Management of overdosage should include general supportive measures to sustain the patient through any period of toxicity that may occur.

DOSAGE AND ADMINISTRATION

Cisplatin Injection is administered by slow intravenous infusion. CISPLATIN INJECTION SHOULD NOT BE GIVEN BY RAPID INTRAVENOUS INJECTION.

Note: Needles or intravenous sets containing aluminum parts that may come in contact with Cisplatin Injection should not be used for preparation or administration. Aluminum reacts with Cisplatin Injection, causing precipitate formation and a loss of potency.

Metastatic Testicular Tumors

The usual Cisplatin Injection dose for the treatment of testicular cancer in combination with other approved chemotherapeutic agents is 20 mg/m^2 IV daily for 5 days per cycle.

Metastatic Ovarian Tumors

The usual Cisplatin Injection dose for the treatment of metastatic ovarian tumors in combination with cyclophosphamide is 75 to 100 mg/m^2 IV per cycle once every four weeks (DAY 1).

The dose of cyclophosphamide when used in combination with Cisplatin Injection is 600 mg/m^2 IV once every 4 weeks (DAY 1).

For directions for the administration of cyclophosphamide, refer to the cyclophosphamide package insert.

In combination therapy, Cisplatin Injection and cyclophosphamide are administered sequentially.

As a single agent, Cisplatin Injection should be administered at a dose of 100 mg/m^2 IV per cycle once every four weeks.

Advanced Bladder Cancer

Cisplatin Injection should be administered as a single agent at a dose of 50 to 70 mg/m^2 IV per cycle once every 3 to 4 weeks depending on the extent of prior exposure to radiation therapy and/or prior chemotherapy. For heavily pretreated patients an initial dose of 50 mg/m^2 per cycle repeated every 4 weeks is recommended.

All Patients

Pretreatment hydration with 1 to 2 liters of fluid infused for 8 to 12 hours prior to a Cisplatin Injection dose is recommended. The drug is then diluted in 2 liters of 5% Dextrose in 1/2 or 1/3 normal saline containing 37.5 g of mannitol, and infused over a 6- to 8-hour period. If diluted solution is not to be used within 6 hours, protect solution from light. Do not dilute Cisplatin Injection in just 5% Dextrose Injection. Adequate hydration and urinary output must be maintained during the following 24 hours.

A repeat course of Cisplatin Injection should not be given until the serum creatinine is below 1.5 mg/100 mL, and/or the BUN is below 25 mg/100 mL. A repeat course should not be given until circulating blood elements are at an acceptable level (platelets ≥100,000/mm^3, WBC ≥4000/mm^3). Subsequent doses of Cisplatin Injection should not be given until an audiometric analysis indicates that auditory acuity is within normal limits.

PREPARATION OF INTRAVENOUS SOLUTIONS

Preparation Precautions

Caution should be exercised in handling the aqueous solution. Procedures for proper handling and disposal of anticancer drugs should be utilized. Several guidelines on this subject have been published.^1-4 To minimize the risk of dermal exposure, always wear impervious gloves when handling vials and IV sets containing cisplatin.

Skin reactions associated with accidental exposure to cisplatin may occur. The use of gloves is recommended. If cisplatin contacts the skin or mucosa, immediately and thoroughly wash the skin with soap and water and flush the mucosa with water. More information is available in the references listed below.

Instructions for Preparation

The aqueous solution should be used intravenously only and should be administered by IV infusion over a 6- to 8-hour period (see DOSAGE AND ADMINISTRATION).

Parenteral drug products should be inspected visually for particulate matter and discoloration prior to administration, whenever solution and container permit.

NOTE TO PHARMACIST: Exercise caution to prevent inadvertent cisplatin overdosage. Please call prescriber if dose is greater than 100 mg/m^2 per cycle. Aluminum and flip-off seal of vial have been imprinted with the following statement:

CALL DR. IF DOSE>100 MG/M^2/CYCLE.

STABILITY

Cisplatin Injection is a sterile, multidose vial without preservatives.

Store at 15° C to 25°C (59° to 77°F). Do not refrigerate. Protect unopened container from light.

The cisplatin remaining in the amber vial following initial entry is stable for 28 days protected from light or for 7 days under fluorescent room light.

HOW SUPPLIED

Cisplatin Injection is available as follows:

NDC 44567-509-01 Each multidose vial contains 50 mg of cisplatin

NDC 44567-510-01 Each multidose vial contains 100 mg of cisplatin

NDC 44567-511-01 Each multidose vial contains 200 mg of cisplatin

REFERENCES

1. NIOSH Alert: Preventing occupational exposures to antineoplastic and other hazardous drugs in healthcare settings. 2004. U.S. Department of Health and Human Services, Public Health Service, Centers for Disease Control and Prevention, National Institute for Occupational Safety and Health, DHHS (NIOSH) Publication No. 2004-165.
2. OSHA Technical Manual, TED 1-0.15A, Section VI: Chapter 2.
  Controlling occupational exposure to hazardous drugs. OSHA, 1999. http://www.osha.gov/dts/osta/otm/otm_vi/otm_vi_2.html.
3. American Society of Health-System Pharmacists. ASHP guidelines on handling hazardous drugs. Am J Health-Syst Pharm. 2006;63:1172-1193.
4. Polovich M, White JM, Kelleher LO, eds. 2005. Chemotherapy and biotherapy guidelines and recommendations for practice. 2nd ed. Pittsburgh, PA: Oncology Nursing Society.

Manufactured for:

WG Critical Care, LLC

Paramus, NJ 07652

Made in Italy

Rev. 04/2015

PRINCIPAL DISPLAY PANEL

CISplatin doses greater than 100 mg/m^2 once
every 3 to 4 weeks are rarely used. See Package Insert.

NDC 44567-509-01 50 mL multidose vial

CISplatin Injection

50 mg/50 mL

(1 mg/mL) Rx only

For Intravenous Use

WG Critical Care

PRINCIPAL DISPLAY PANEL

CISplatin doses greater than 100 mg/m^2 once
every 3 to 4 weeks are rarely used. See Package Insert.

NDC 44567-510-01 100 mL multidose vial

CISplatin Injection

100 mg/100 mL

(1 mg/mL) Rx only

For Intravenous Use WG Critical Care

PRINCIPAL DISPLAY PANEL

CISplatin doses greater than 100 mg/m^2 once
every 3 to 4 weeks are rarely used. See Package Insert.

NDC 44567-511-01 200 mL multidose vial

CISplatin Injection

200 mg/200 mL

(1 mg/mL) Rx only

For Intravenous Use WG Critical Care